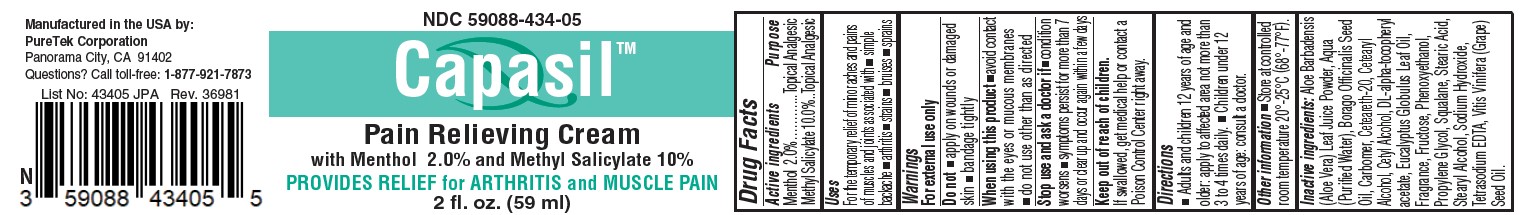 DRUG LABEL: Capasil
NDC: 59088-434 | Form: CREAM
Manufacturer: PureTek Corporation
Category: otc | Type: HUMAN OTC DRUG LABEL
Date: 20241001

ACTIVE INGREDIENTS: METHYL SALICYLATE 100 mg/1 mL; MENTHOL 20 mg/1 mL
INACTIVE INGREDIENTS: MENHADEN OIL; PROPYLENE GLYCOL; AMINOMETHYL PROPANEDIOL; LIMONENE, (+)-; PALMITIC ACID; POLYOXYL 20 CETOSTEARYL ETHER; ALOE VERA LEAF; BORAGE SEED OIL; CARBOMER HOMOPOLYMER TYPE B (ALLYL SUCROSE CROSSLINKED); CETOSTEARYL ALCOHOL; CETYL ALCOHOL; EUCALYPTUS OIL; FRUCTOSE; PHENOXYETHANOL; WATER; SQUALANE; STEARIC ACID; STEARYL ALCOHOL; EDETATE SODIUM; .ALPHA.-TOCOPHEROL ACETATE, DL-; GRAPE SEED OIL

Capasil

Active ingredients

Menthol 2.0%………... Topical Analgesic
Methyl Salicylate 10%…Topical Analgesic

Purpose

Topical Analgesic

Keep out of reach of children.

If swallowed, get medical help or contact a Poison Control Center right away.

Uses

For the temporary relief of minor aches and pains of muscles and joints associated with simple backache, arthritis, strains, bruises, sprains.

Warnings

For external use only.

Do not

- apply on wounds or damaged skin
- bandage tightly

When using this product

avoid contact with the eyes

Stop use and ask a doctor if

- condition worsens
- symptoms persist for more than 7 days or clear up and occur again within a few days

Directions

Adults and children 2 years of age and older: apply to affected area not more than 3 to 4 times daily.

Children under 2 years of age: consult a doctor.

Inactive ingredients

Aloe Barbadensis(Aloe Vera) Leaf Juice Powder, Aqua (Purified Water), Borago Officinalis Seed
Oil, Carbomer, Ceteareth-20, Cetearyl Alcohol, Cetyl Alcohol, DL-alpha-tocopheryl
acetate, Eucalyptus Globulus Leaf Oil, Fragrance, Fructose, Phenoxyethanol,
Propylene Glycol, Squalane, Stearic Acid, Stearyl Alcohol, Sodium Hydroxide,
Tetrasodium EDTA, Vitis Vinifera (Grape) Seed Oil.

STORAGE AND HANDLING

Store at controlled room temperature 20°-25°C (68°-77°F).